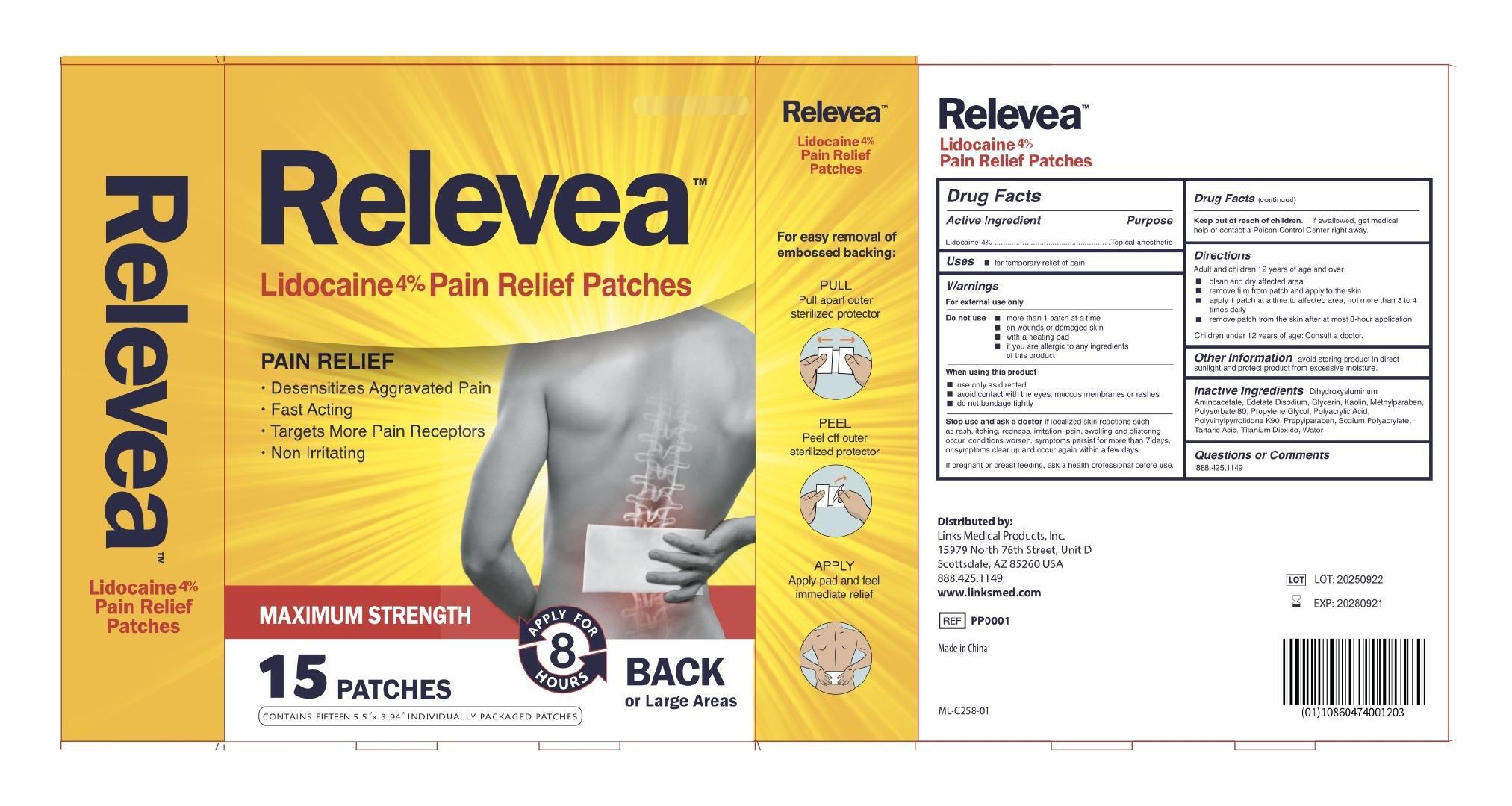 DRUG LABEL: Relevea Pain Relief Patch
NDC: 51028-004 | Form: PATCH
Manufacturer: Links Medical Products
Category: otc | Type: HUMAN OTC DRUG LABEL
Date: 20250821

ACTIVE INGREDIENTS: LIDOCAINE 40 mg/1 g
INACTIVE INGREDIENTS: SODIUM POLYACRYLATE (2500000 MW); DIHYDROXYALUMINUM AMINOACETATE; KAOLIN; METHYLPARABEN; POLYACRYLIC ACID (250000 MW); WATER; TARTARIC ACID; PROPYLENE GLYCOL; PROPYLPARABEN; EDETATE DISODIUM; GLYCERIN; POVIDONE K90; TITANIUM DIOXIDE; POLYSORBATE 80

Relevea Pain Relief Patch

ACTIVE INGREDIENT

Lidocaine 4%

PURPOSE

Topical anesthetic

USES

for temporary relief of pain

WARNINGS

For external use only

Do not use

- more than 1 patch at a time
- on wounds or damaged skin
- with a heating pad
- if you are allergic to any ingredients of this product

When using this product

- use only as directed
- avoid contact with the eyes, mucous membranes or rashes
- do not bandage

Stop use and ask a doctor if

localized skin reactions such as rash, itching, redness, irritation, pain, swelling and blistering occur, conditions worsen, symptoms persist for more than 7 days, or symptoms clear up and occur again within a few days.

If pregnant or breast feeding, ask a health professional before use.

Keep out of reach of children

If swallowed, get medical help or contact a Poison Control Center right away.

DIRECTIONS

Adult and children 12 years of age and over:

- clean and dry affected area
- remove film from patch and apply to the skin
- apply 1 patch at a time to affected area, not more than 3 to 4 times daily
- remove patch from the skin after at most 8-hour application

Children under 12 years of age: Consult a doctor

OTHER INFORMATION

avoid storing product in direct sunlight and protect product from excessive moisture.

INACTIVE INGREDIENTS

Dihydroxyaluminum Aminoacetate, Edetate Disodium, Glycerin, Kaolin, Methylparaben, Polysorbate 80, Propylene Glycol, Polyacrylic Acid, Polyvinylpyrrolidone K90, Propylparaben, Sodium Polyacrylate, Tartaric Acid, Titanium Dioxide, Water

Questions or Comments

888.425.1149